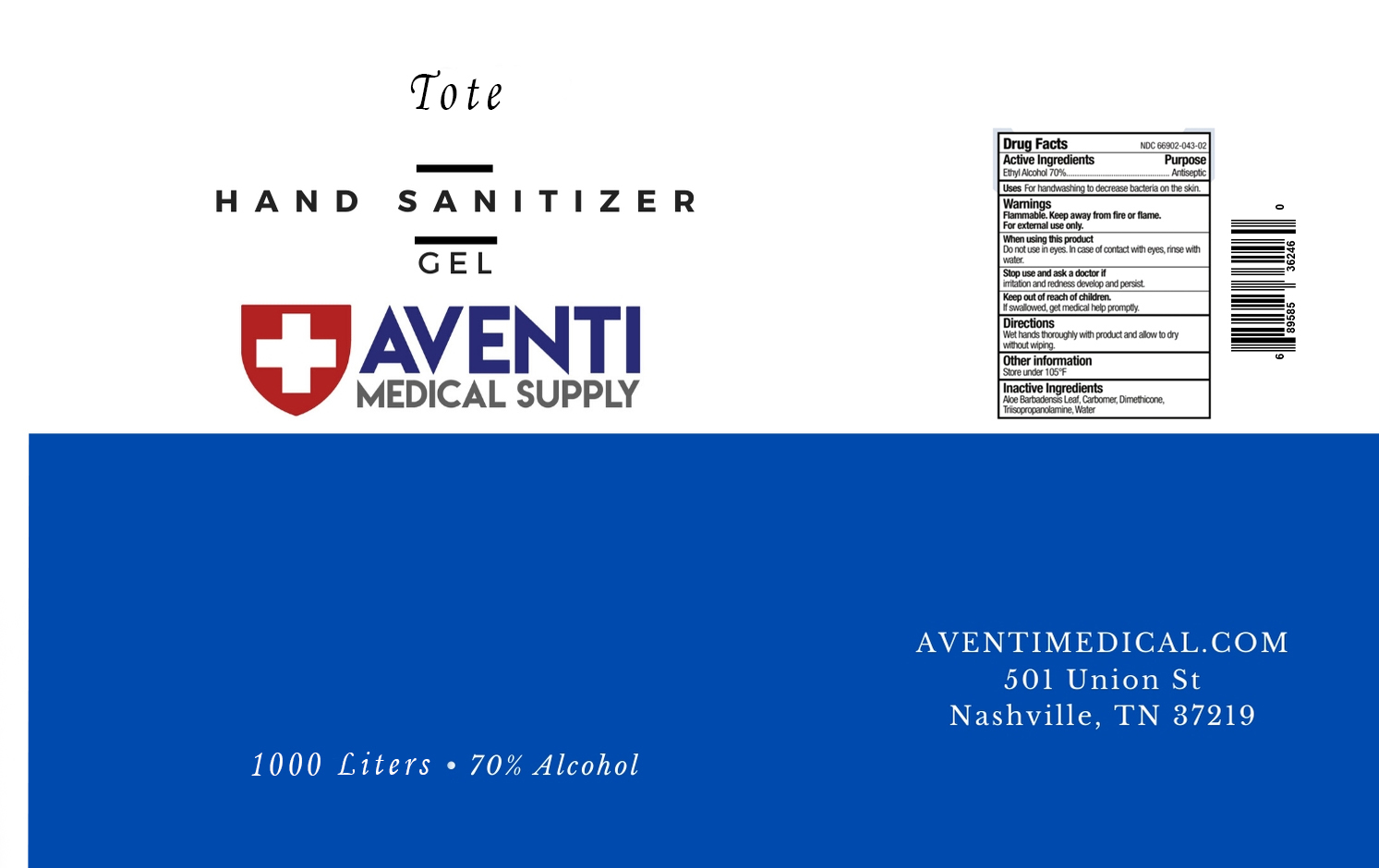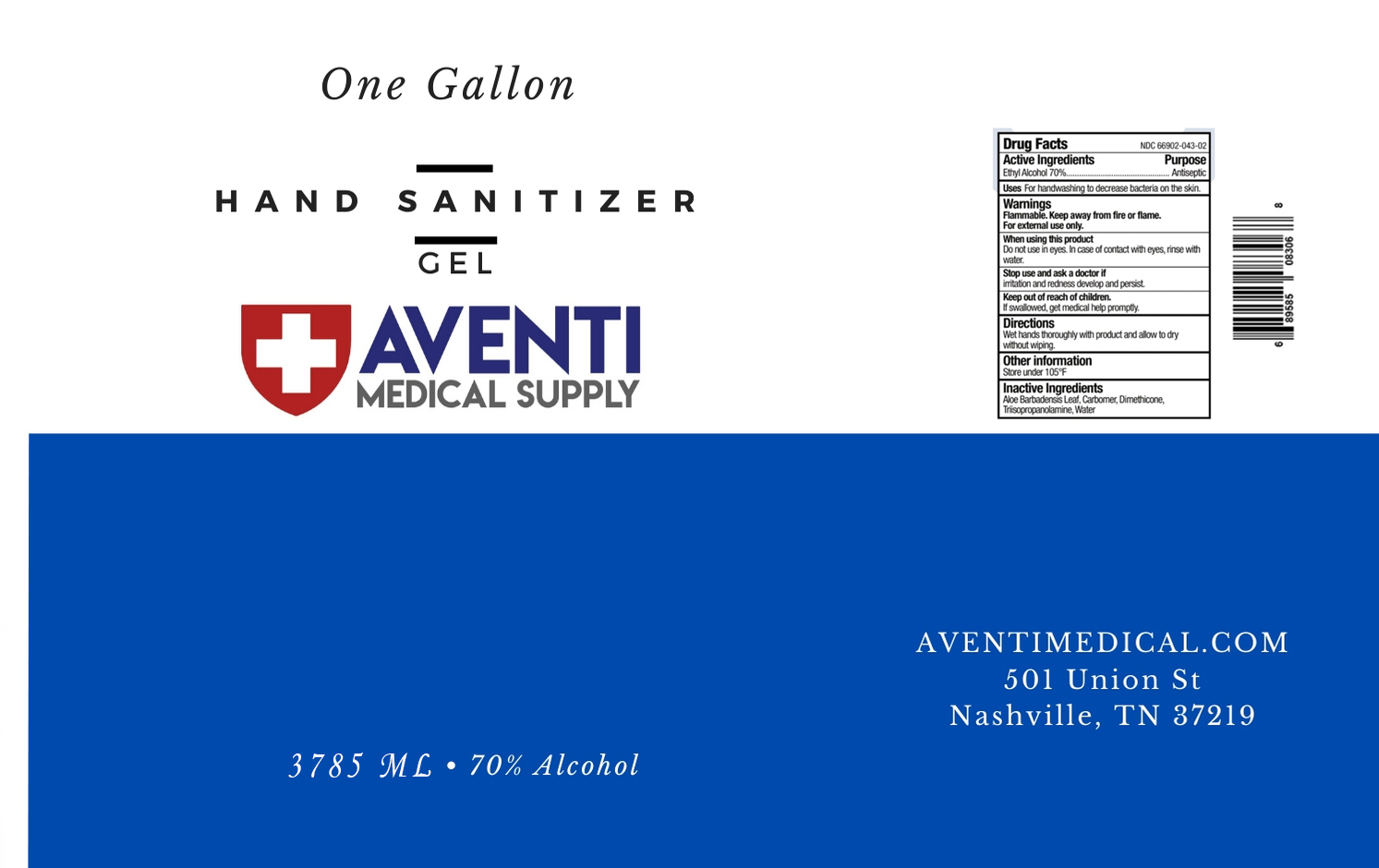 DRUG LABEL: Hand Sanitizer
NDC: 77811-001 | Form: GEL
Manufacturer: Aventi Medical, LLC
Category: otc | Type: HUMAN OTC DRUG LABEL
Date: 20200523

ACTIVE INGREDIENTS: ALCOHOL 0.7 mL/1 mL
INACTIVE INGREDIENTS: ALOE VERA LEAF; CARBOMER HOMOPOLYMER, UNSPECIFIED TYPE; DIMETHICONE; TRIISOPROPANOLAMINE; WATER

Hand Sanitizer

Active ingredients

Ethyl Alcohol 70%

Purpose

Antiseptic

Uses

For handwashing to decrease bacteria on the skin.

Warnings

Flammable. Keep away from fire or flame. For external use only.

When using this product

Do not use in eyes. In case of contact with eyes, rinse with water.

Stop use and ask a doctor

if irritation and redness develop and persist.

Keep out of reach of children.

If swallowed, get medical help promptly.

Directions

Wet hands thoroughly with product and allow to dry without wiping.

Other information

Store under 105oF

Inactive ingredients

Aloe Barbadensis Leaf, Carbomer, Dimethicone, Triisopropanolamine, Water